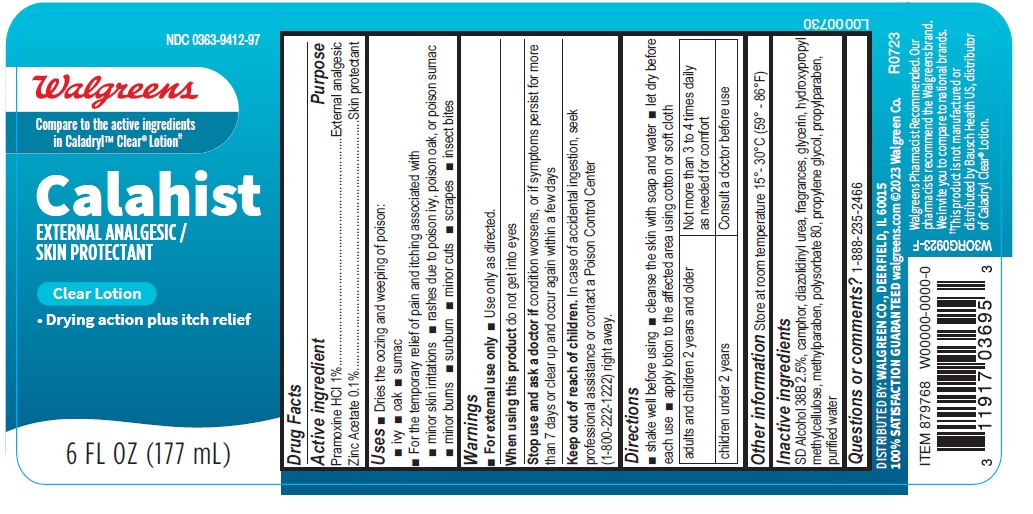 DRUG LABEL: calahist clear
NDC: 0363-9412 | Form: LOTION
Manufacturer: WALGREEN COMPANY
Category: otc | Type: HUMAN OTC DRUG LABEL
Date: 20231027

ACTIVE INGREDIENTS: PRAMOXINE HYDROCHLORIDE 10 mg/1 mL; ZINC ACETATE 1 mg/1 mL
INACTIVE INGREDIENTS: PROPYLPARABEN; POLYSORBATE 80; CAMPHOR (NATURAL); DIAZOLIDINYL UREA; GLYCERIN; HYPROMELLOSE, UNSPECIFIED; METHYLPARABEN; WATER; PROPYLENE GLYCOL

walgreen-Calahist Clear Lotion

Active ingredient

Pramoxine HCI 1%

Zinc Acetate 0.1%

Purpose

External analgesic

Skin protectant

Uses

■ Dries the oozing and weeping of poison:
■ ivy ■ oak ■ sumac
■ For the temporary relief of pain and itching associated with
■ minor skin irritations ■ rashes due to poison ivy, poison oak, or poison sumac
■ minor burns ■ sunburn ■ minor cuts ■ scrapes ■ insect bites

Warnings

■ For external use only ■ Use only as directed.

When using this product

do not get into eyes

Stop use and ask a doctor if

condition worsens, or if symptoms persist for more than 7 days or clear up and occur again within a few days

Keep out of reach of children.

In case of accidental ingestion, seek professional assistance or contact a Poison Control Center (1-800-222-1222) right away.

Directions

■ shake well before using ■ cleanse the skin with soap and water ■ let dry before each use ■ apply lotion to the affected area using cotton or soft cloth

adults and children 2 years and older | Not more than 3 to 4 times daily as needed for comfort
children under 2 years | Consult a doctor before use

Other information

Store at room temperature 15°- 30°C (59° - 86°F)

Inactive ingredients

SD Alcohol 38B 2.5%, camphor, diazolidinyl urea, fragrances, glycerin, hydroxypropyl methylcellulose, methylparaben, polysorbate 80, propylene glycol, propylparaben, purified water

Questions or comments?

1-888-235-2466

DISTRIBUTED BY: WALGREEN CO., DEERFIELD, IL 60015
100% SATISFACTION GUARANTEED walgreens.com ©2023 Walgreen Co.

Walgreens Pharmacist Recommended. Our pharmacists recommend the Walgreens brand.
We invite you to compare to national brands.
††This product is not manufactured or distributed by Bausch Health US, distributor of Caladryl Clear® Lotion.

L0000730

R0723

177 mL Bottle Label

NDC 0363-9412-97

Walgreens

Compare to the active ingredients
in Caladryl™ Clear® Lotion††

Calahist

EXTERNAL ANALGESIC /
SKIN PROTECTANT

Clear Lotion

• Drying action plus itch relief

6 FL OZ (177 mL)